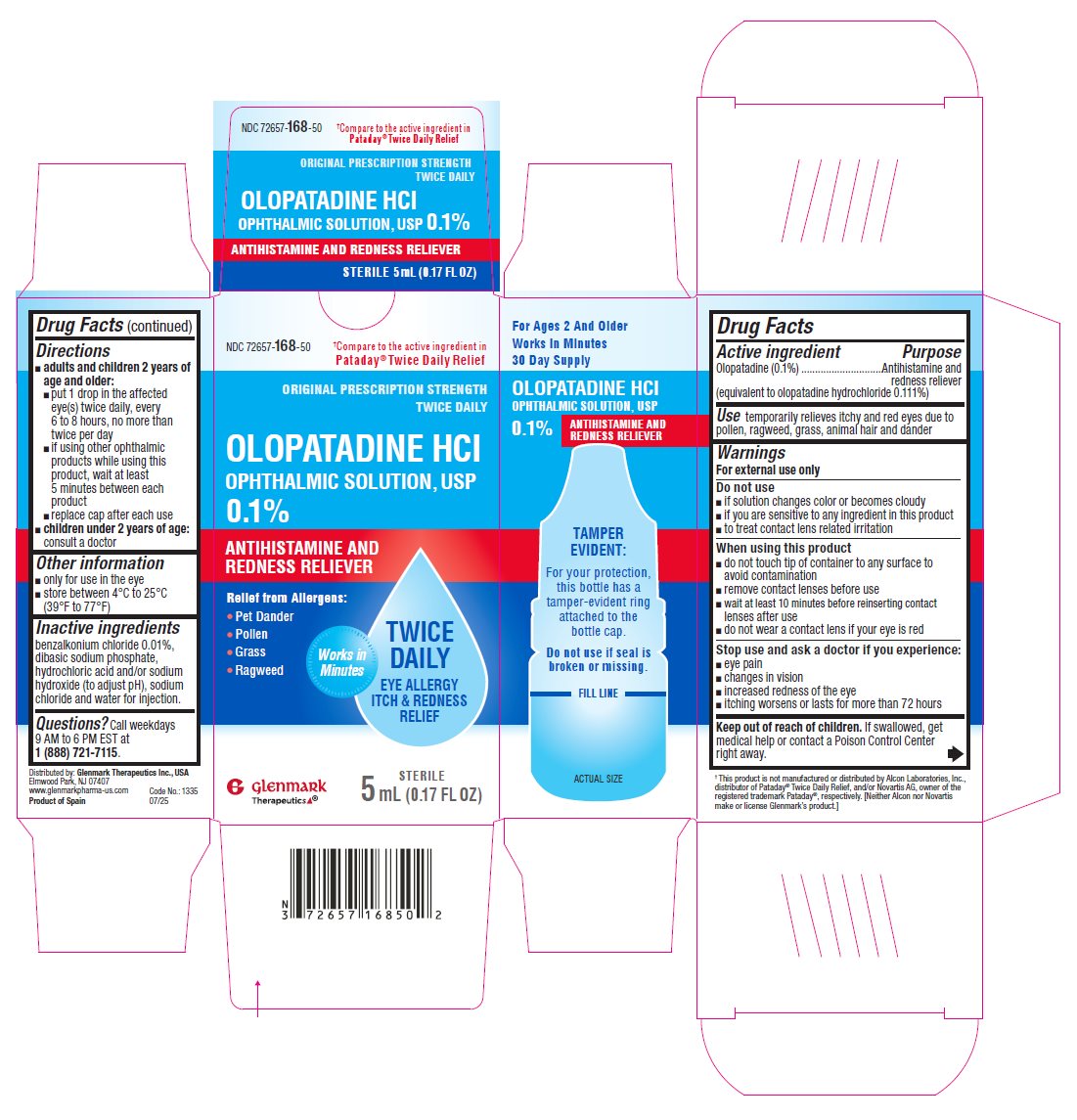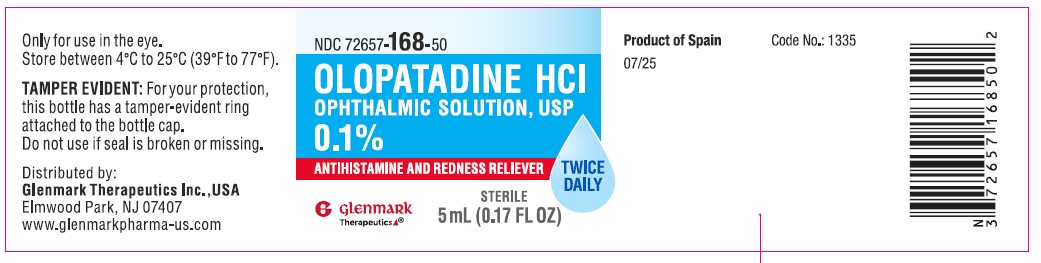 DRUG LABEL: OLOPATADINE HYDROCHLORIDE
NDC: 72657-168 | Form: SOLUTION
Manufacturer: GLENMARK THERAPEUTICS INC., USA
Category: otc | Type: HUMAN OTC DRUG LABEL
Date: 20260127

ACTIVE INGREDIENTS: OLOPATADINE HYDROCHLORIDE 1 mg/1 mL
INACTIVE INGREDIENTS: BENZALKONIUM CHLORIDE; HYDROCHLORIC ACID; SODIUM CHLORIDE; SODIUM HYDROXIDE; SODIUM PHOSPHATE, DIBASIC, ANHYDROUS; WATER

Drug Facts

ACTIVE INGREDIENT

Active Ingredient | Purpose
Olopatadine (0.1%). (equivalent to olopatadine hydrochloride 0.111%) | Antihistamine and redness reliever

Uses

temporarily relieves itchy and red eyes due to pollen, ragweed, grass, animal hair and dander

Warnings
For external use only

Do not use

- if solution changes color or becomes cloudy
- if you are sensitive to any ingredient in this product
- to treat contact lens related irritation

When using this product

- do not touch tip of container to any surface to avoid contamination
- remove contact lenses before use
- wait at least 10 minutes before reinserting contact lenses after use
- do not wear a contact lens if your eye is red

Stop use and ask a doctor if you experience:

- eye pain
- changes in vision
- increased redness of the eye
- itching worsens or lasts for more than 72 hours

Keep out of reach of children. If swallowed, get medical help or contact a Poison Control Center right away.

Directions

- adults and children 2 years of age and older:
- put 1 drop in the affected eye(s) twice daily, every 6 to 8 hours, no more than twice per day
- if using other ophthalmic products while using this product, wait at least 5 minutes between each product
- replace cap after each use
- children under 2 years of age: consult a doctor

Other information

- only for use in the eye
- store between 4°C to 25°C (39°F to 77°F)

Inactive ingredients

benzalkonium chloride 0.01%, dibasic sodium phosphate, hydrochloric acid and/ or sodium hydroxide (to adjust PH), sodium chloride and water for injection.

Questions or comments?

Call weekdays 9 AM to 6 PM EST at 1 (888) 721-7115.

Distributed by:

Glenmark Therapeutics Inc., USA

Elmwood Park, NJ 07407

Product of Spain

07/25

PRINCIPAL DISPLAY PANEL

NDC 72657-168-50

Olopatadine HCl Ophthalmic Solution, USP 0.1%
Antihistamine and Redness Reliever

Twice Daily Relief
Eye Allergy Itch & Redness Relief

STERILE

5 mL (0.17 FL OZ)

NDC 72657-168-50

Olopatadine HCl Ophthalmic Solution,USP 0.1%
Antihistamine and Redness Reliever

Twice Daily

STERILE
5 mL (0.17 FL OZ)